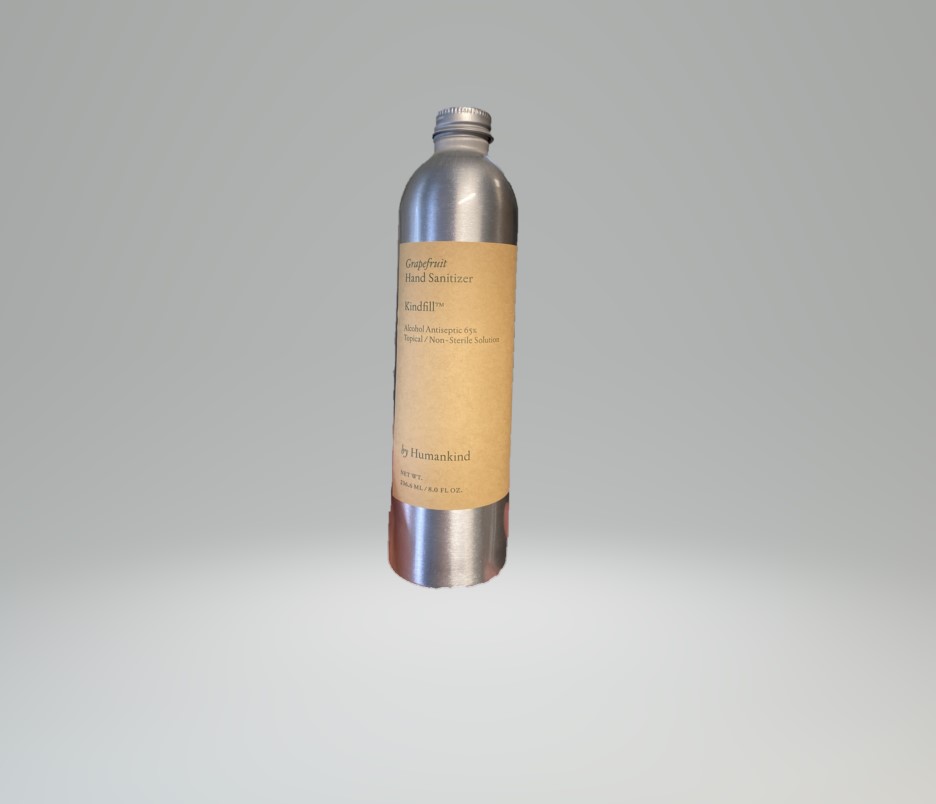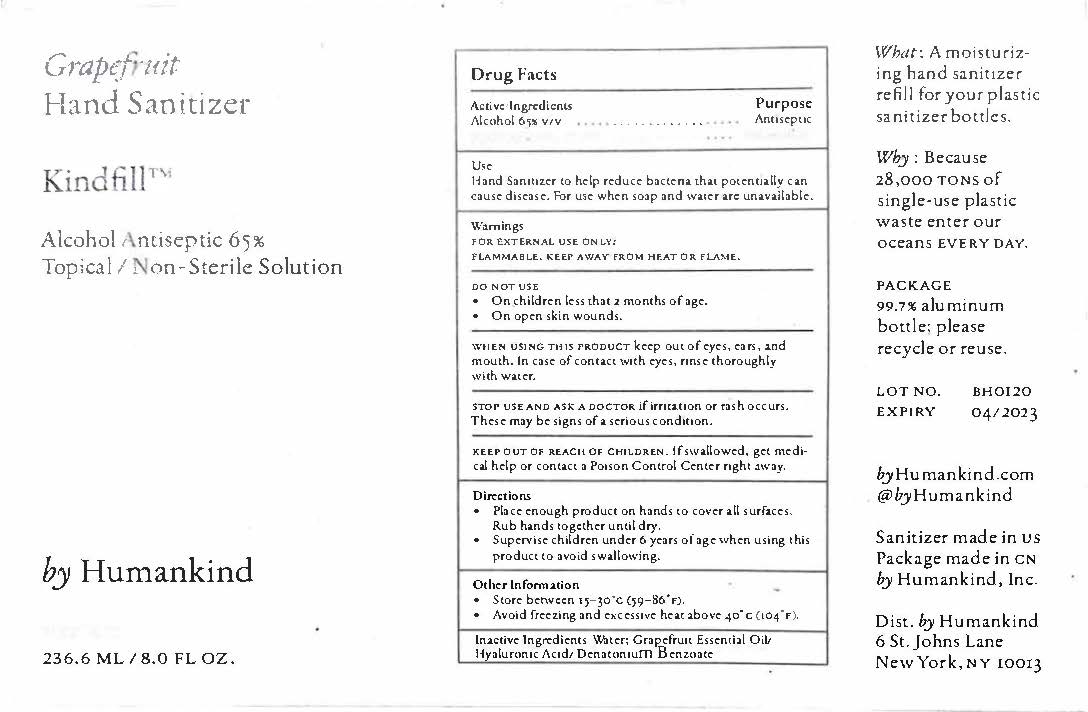 DRUG LABEL: Hand Sanitizer
NDC: 73953-0101 | Form: GEL
Manufacturer: Doerfler Manufacturing Inc
Category: otc | Type: HUMAN OTC DRUG LABEL
Date: 20200331

ACTIVE INGREDIENTS: ALCOHOL 65 mL/100 mL
INACTIVE INGREDIENTS: WATER 34 mL/100 mL; HYALURONIC ACID 2 g/100 mL; GRAPEFRUIT OIL 1 mL/100 mL; DENATONIUM BENZOATE 0.00004 mL/100 mL

Active Ingredients

Alcohol 65% v/v Purpose: Antiseptic

Use

Hand Sanitizer helps reduce bacteria on skin

Warnings

For external use only

Flammable. Keep away from heat or flame

Do not use

On children less than 2 month of age

On open skin wounds

When using this product

do not use in or near eyes. In case of contact with eyes, rinse with water.

Stop use and ask a doctor

If irritation or rash occurs and stays.

Keep out of reach of children

If swallowed, get medical help of contact Poison Control Center right away.

Directions

Place enough product on hands to cover all surfaces. Rub hand together until dry

Supervise children unde 6 years of age when using this product to avoid swallowing.

Directions

Place enough product on hands to cover all surfaces. Rub hand together until dry

Other information

Stay below 110 F (43C)

May discolor certain fabrics or surfaces

Inactive ingredients

Water, Bergamot Essential Oil, Lemon Essential Oil, Lime Essential Oil, Hyaluronic Acid

Hand Sanitizer

Grapefruit

Hand Santizier

Kindfill

Alcohol Antiseptic 65%

byHumankind

236.6 ML/8.0 FL OZ